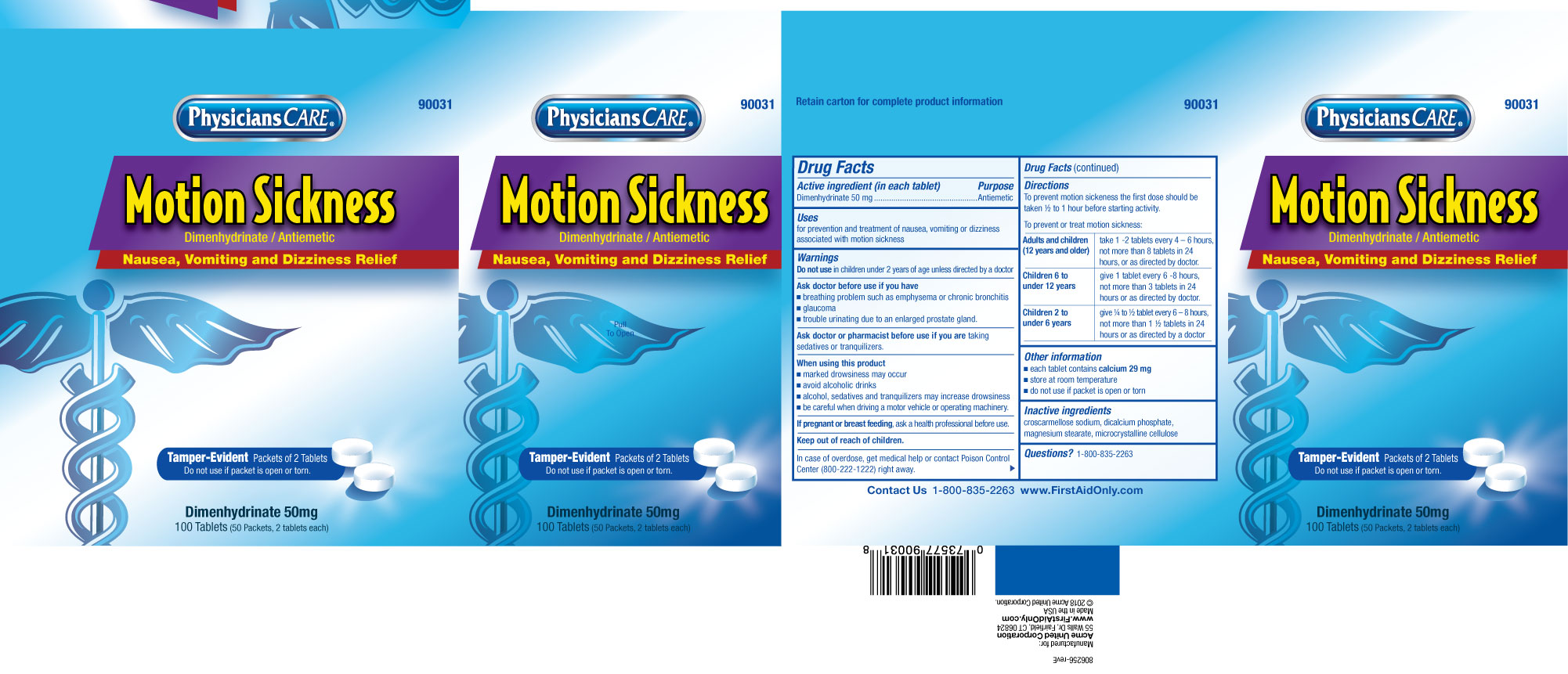 DRUG LABEL: Dimenhydrinate
NDC: 0924-1007 | Form: TABLET
Manufacturer: Acme United Corporation
Category: otc | Type: HUMAN OTC DRUG LABEL
Date: 20201117

ACTIVE INGREDIENTS: DIMENHYDRINATE 50 mg/1 1
INACTIVE INGREDIENTS: CROSCARMELLOSE SODIUM; DIBASIC CALCIUM PHOSPHATE DIHYDRATE; MAGNESIUM STEARATE; MICROCRYSTALLINE CELLULOSE

1006-Acme

Drug Facts

Active Ingredient (in each tablet)

Dimenhydrinate 50 mg

Purpose

Antiemetic

Uses

for prevention and treatment of nausea, vomiting or dizziness associated with motion sickness

WARNINGS

Do not use in children under 2 years of age unless directed by a doctor

Ask doctor before use if you have

- breathing problem such as emphysema or chronic bronchitis
- glaucoma
- trouble urinating due to an enlarged prostate gland.

Ask doctor or pharmacist before use if you are taking sedatives or tranquilizers.

When using this product

- marked drowsiness may occir
- avoid alcoholic drinks
- alcohol, sedatives and traquilizers may increase drowsiness
- be careful when driving a motor vehicle or operating machinery

PREGNANCY OR BREAST FEEDING

If pregnant or breast feeding, ask a helath professional before use.

Keep out of reach of children.

OVERDOSAGE

In case of overdose, get medical help or contact Poison Control Center (800-222-1222) right away.

Directions

To prevemt motion sickness the first dose should be taken ½ to 1 hour before starting activity.

To prevent or treat motion sickness:

Adults and Children (12 years and older) | take 1-2 tablets every 4-6 hours, not more than 8 tablets in 24 hours, or as directed by doctor.
Children 6 to under 12 years | give 1 tablet every 6-8 hours, not more than 3 tablets in 24 hours or as directed by doctor.
Children 2 to under 6 years | give ¼ to ½ tablet every 6-8 hours, not more than 1½ tablets in 24 hours or as directed by a doctor

Other information

- each tablet contains calcium 29 mg
- store at room temperature
- do not use if packet is open or torn

INACTIVE INGREDIENT

croscarmellose sodium, dicalcium phosphate, magnesium stearate, microcrystalline cellulose

Questions?

1-800-835-2263

Retain carton for complete product information

Manufactured for:

Acme United Corporation

55 Walls Dr, Fairfield, CT 06824

www.FirstAidOnly.com

Made in the USA

©2018 Acme United Corporation

PACKAGE LABEL

Physician Care®

Motion Sickness

Dimenhydrinate/ Antiemetic

Nausea, Vomiting and Dizziness Relief

Tamper-Evident Packets of 2 Tablets

Do not use if packet is open or torn.

Dimenhydrinate 50mg

100 Tablets (50 Packets, 2 Tablets each)